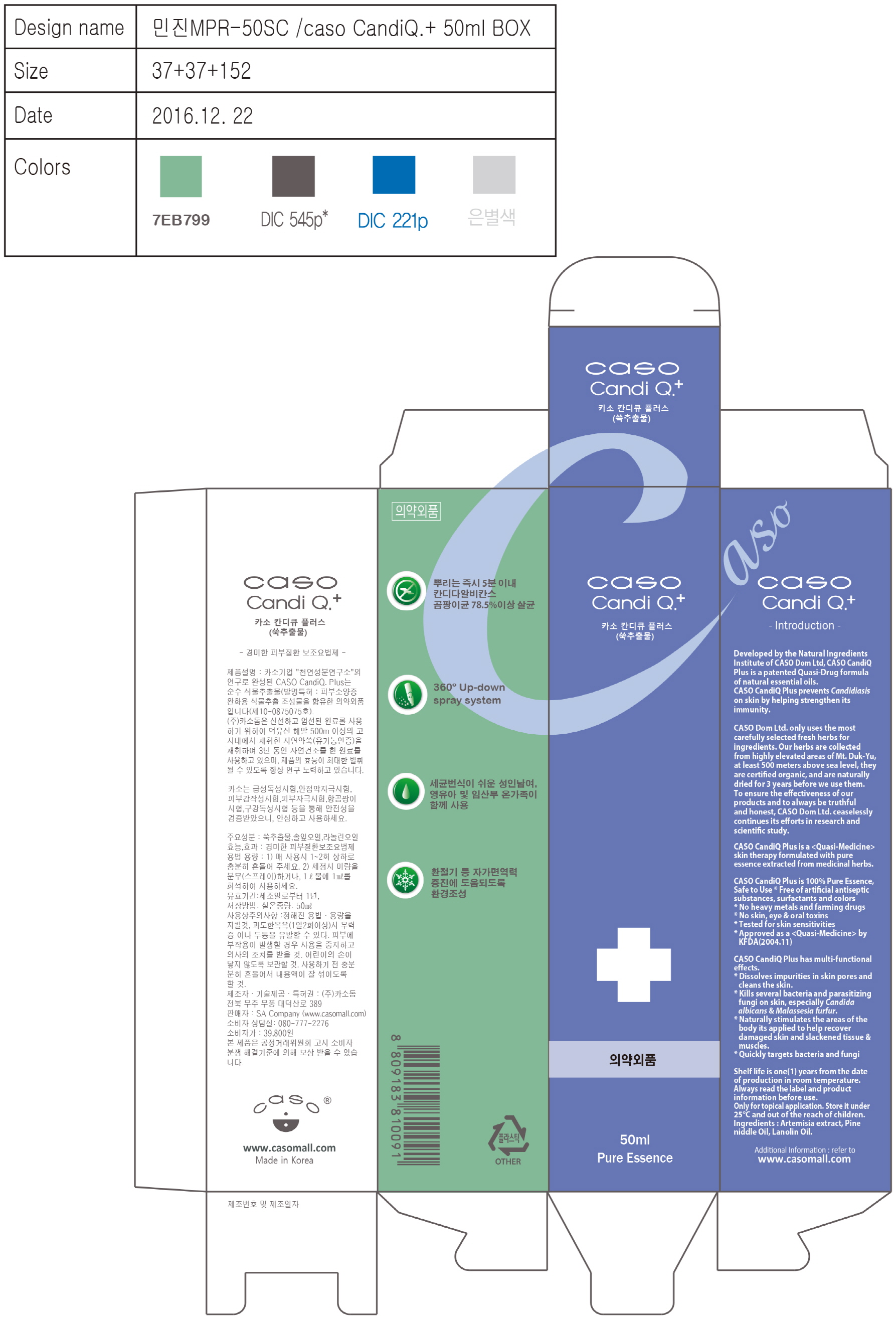 DRUG LABEL: CASO CANDIQ. PLUS
NDC: 71581-0002 | Form: LIQUID
Manufacturer: CASO Dom Ltd.
Category: otc | Type: HUMAN OTC DRUG LABEL
Date: 20170719

ACTIVE INGREDIENTS: WORMWOOD 96.6 g/100 mL
INACTIVE INGREDIENTS: LANOLIN OIL; PINE NEEDLE OIL (PINUS SYLVESTRIS)

Drug Facts

ACTIVE INGREDIENT

Artemisia Montana Pampan Extract (Wormwood)

INACTIVE INGREDIENT

Pine needle oil, Lanolin oil

PURPOSE

Skin protectant

keep out of reach of the children

INDICATIONS AND USAGE

Shake well before every use.

Spray a little on the needed spots.

WARNINGS

•Precautions when using

1. After using or using cosmetics, consult a specialist if you have any abnormal symptoms such as red spots, swelling or itching or side effects caused by direct sunlight.

2. Do not use on wounded area

3. storage and handling Precautions

a) Keep out of the reach of children

b) Store away from direct sunlight.

DOSAGE AND ADMINISTRATION

for external use only